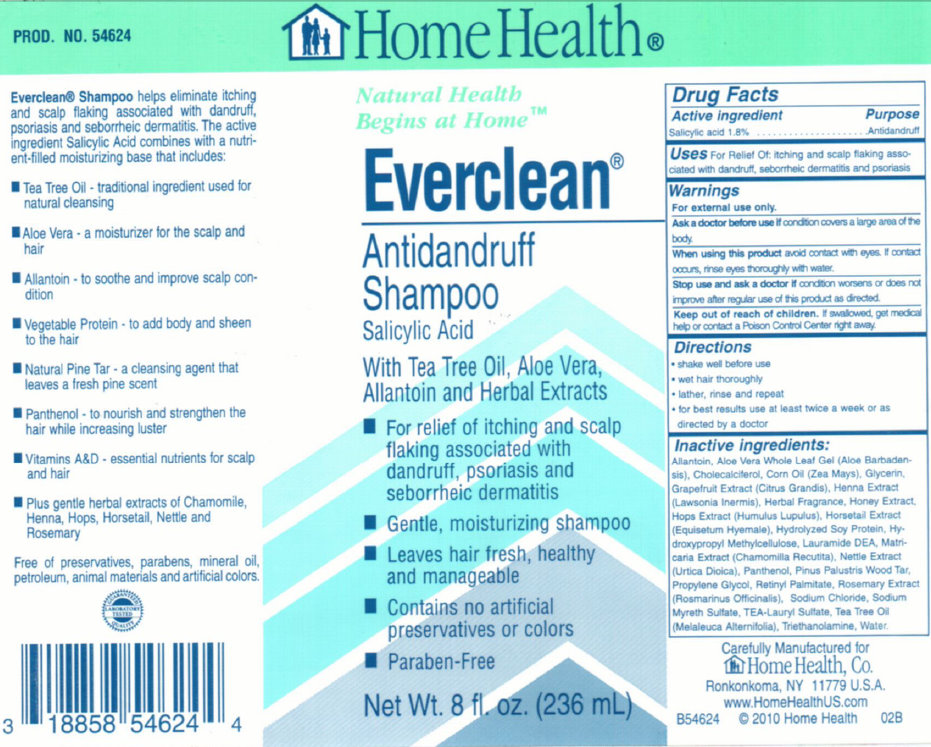 DRUG LABEL: Home Health Everclean Antidandruff
NDC: 76020-200 | Form: SHAMPOO
Manufacturer: Home Health
Category: otc | Type: HUMAN OTC DRUG LABEL
Date: 20231105

ACTIVE INGREDIENTS: SALICYLIC ACID 1.8 g/100 mL
INACTIVE INGREDIENTS: ALLANTOIN; ALOE VERA LEAF; CHOLECALCIFEROL; CORN OIL; GLYCERIN; PUMMELO; LAWSONIA INERMIS LEAF; HONEY; HOPS; LAURIC DIETHANOLAMIDE; CHAMOMILE; URTICA DIOICA LEAF; PANTHENOL; PROPYLENE GLYCOL; VITAMIN A PALMITATE; ROSEMARY; SODIUM CHLORIDE; TRIETHANOLAMINE LAURYL SULFATE; TEA TREE OIL; TROLAMINE; WATER

Home Health Everclean Antidandruff Shampoo

Active ingredient Purpose

Salicylic acid 1.8% ..............Antidandruff

PURPOSE

Uses For Relief Oil; itching and scalp falking associated with dandruff, seborrheic dermatitis and psoriasis

Warnings For external use only.

Ask a doctor before use if condition covers a large of the body.

When using this product avoid contact with eyes. If contact occurs, rinse eyes thoroughly with water.

Stop use and ask a doctor if condition worsens or does not improve after regular use of this product as directed.

Keep out of reach of children. If swallowed, get medical help or contact a Poison Control Center right away.

DOSAGE AND ADMINISTRATION

Directions -Shake well before use -wet hair thoroughly -lather, rinse and repeat -for best results use at least twice a week or as directed by a doctor

INACTIVE INGREDIENT

Inactive ingredients: Allantoin, Aloe Vera Whole Leaf Gel (Aloe Barbadensis), Cholecalciferol, Corn Oil (Zea Mays), Glycerin, Grapefruit Extract (Citrus Grandis), Henna Extract (Lawsonia Inermis), Herbal Fragrance, Honey Extract, Hops Extract (Humulus Lupulus), Horsetail Extract (Equiseturn Hyermale), Hydrolyzed Soy Protein, Hydroxypropyl Methylcellulose, Lauramide DEA, Matricaria Extract (Chamomilla Recutita), Nettle Extract (Urtica Diolca), Panthenol, Pinus Palustris Wood Tar, Propylene Glycol, Retinyl Palmitate, Rosemary Extract (Rosemarinus Officinalis), Sodium Chloride, Sodium Myreth Sulfate, TEA-Lauryl Sulfate, Tea Tree Oil (Melaleuca Alternifolia), Triethanolamine, Water.

DESCRIPTION

PROD. NO. 54624 Everclean Shampoo helps eliminate itching and scalp flacking associated with dandruff, psoriasis and seborrheic dermatitis, The active ingredient Salicylic Acid combines with a nutrient-filled moisturizing base that includes; -Tea Tree Oil - traditional ingredient used for natural cleansing -Aloe Vera - a moisturizer for the scalp and hair - Allantoin - to soothe and improve scalp condition - Vegetable Protein - to add body and sheen to the hair - Natural Pine Tar - a cleansing agent that leaves a fresh pine scent - Panthenol - to nourish and strengthen the hair while increasing luster - Vitamins A and D - essential nutrients for scalp and hair - Plus gentle herbal extracts of Chamomile, Henna, Hops, Horsetail, Nettle and Rosemary Free of preservatives, parabens, mineral oil, petroleum, animal materials and artificial colors. 3 18858 54624 4 Carefully Manufactured for Home Health,Co. Ronkonkoma, NY 11779 U.S.A. www.HomeHealthUS.com B54624 C2010 Home Health 02B

PACKAGE LABEL

HomeHealth Natural Health Begins at Home Everclean Antidandruff Shampoo Salicyclic Acid With Tea Tree Oil, Aloe Vera, Allantoin and Herbal Extracts - For relief of itching and scalp flaking associated with dandruff, psoriasis and seborrheic dermatitis. - Gentle, moisturizing shampoo -Leaves hair fresh, healthy and manageable - Contains no artificial preservatives or colors - Paraben-Free Net Wt. 8 fl. oz (236 mL)